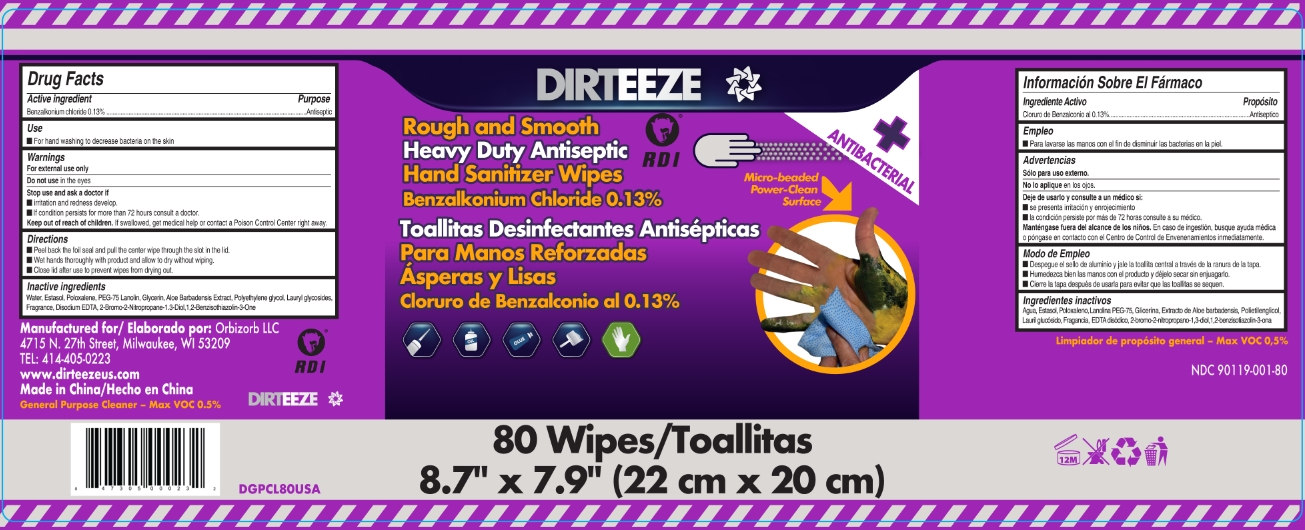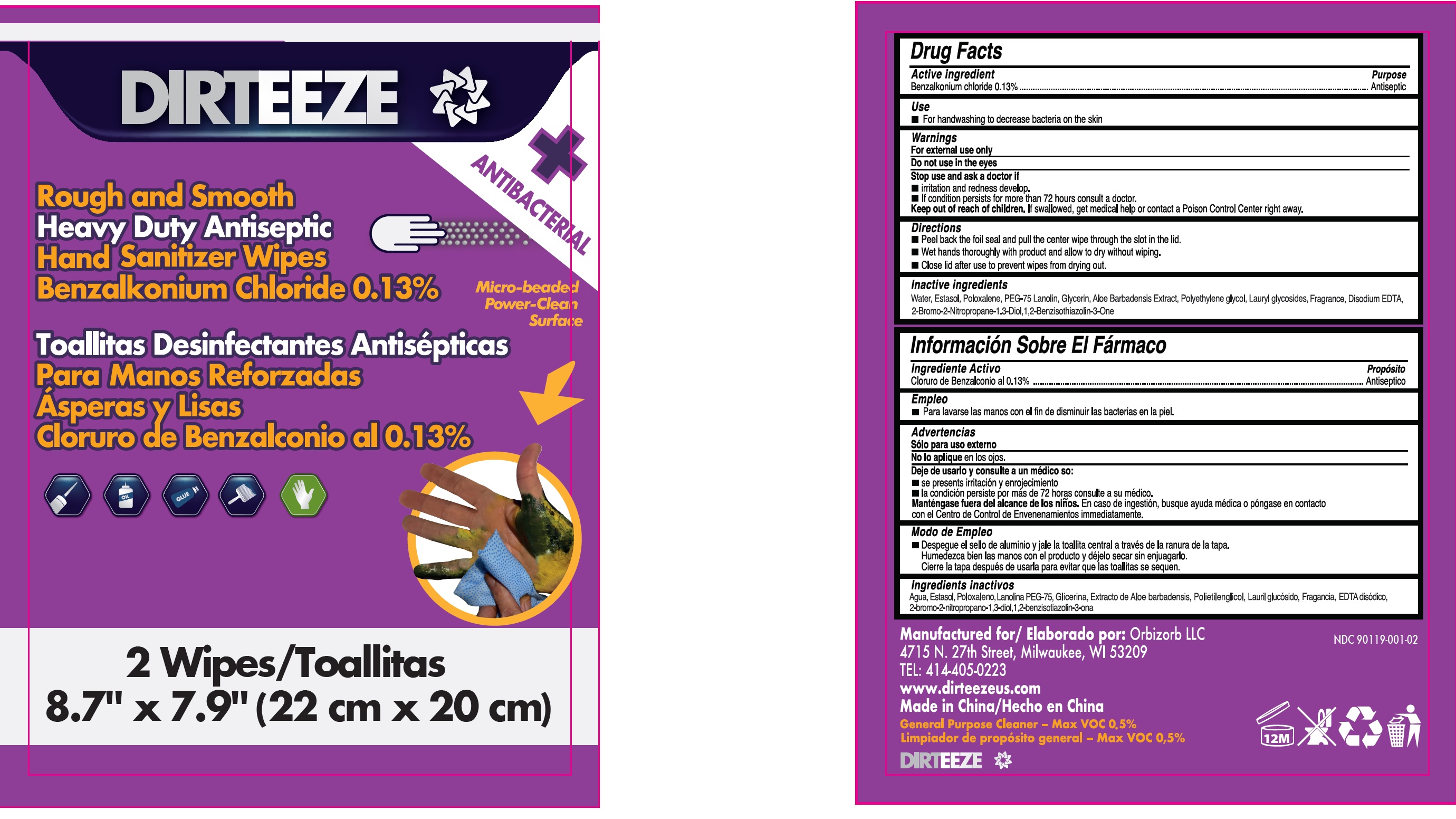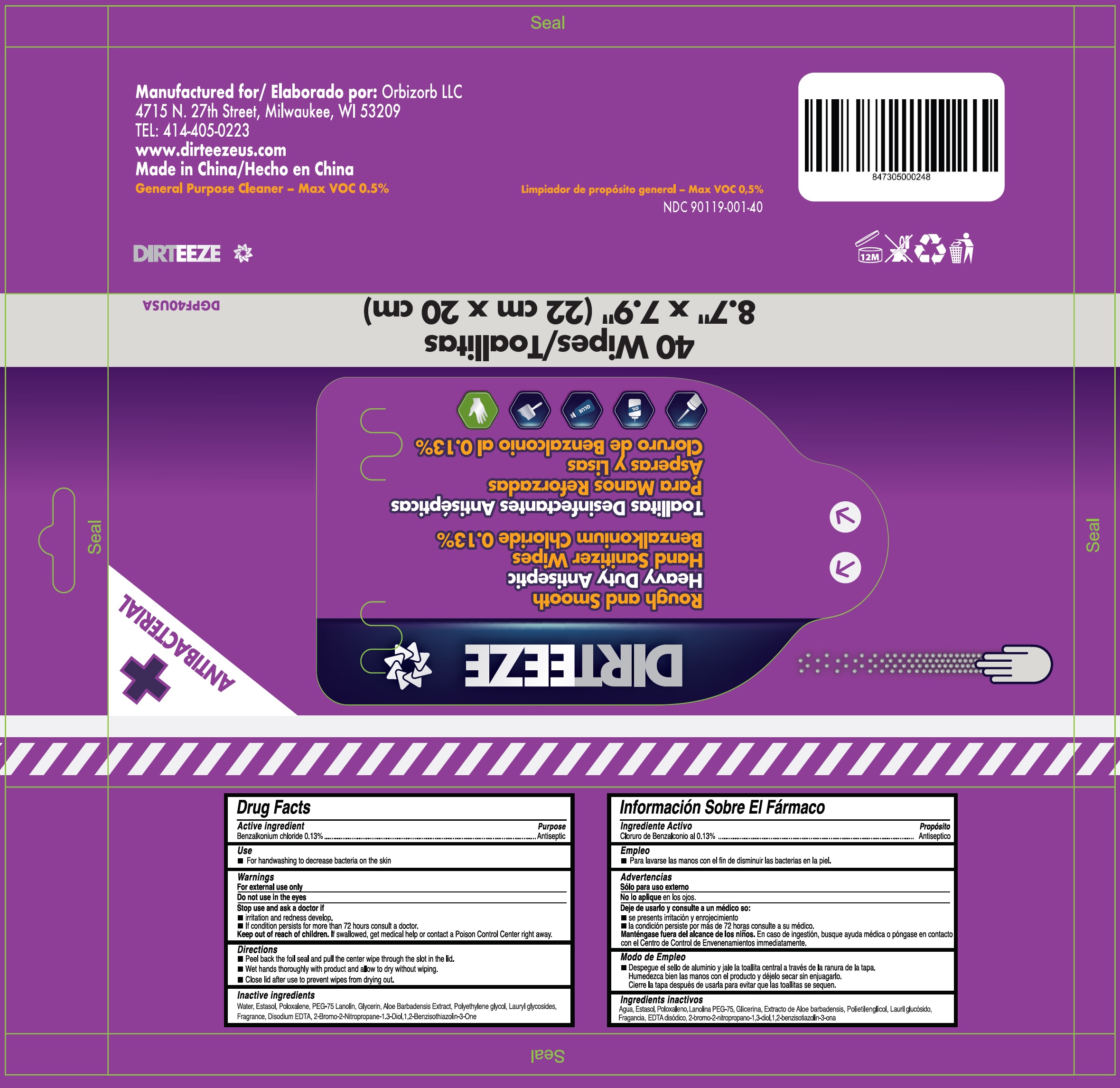 DRUG LABEL: Rough and Smooth Heavy Duty Antiseptic Hand Sanitizer
NDC: 90119-001 | Form: CLOTH
Manufacturer: Orbizorb LLC
Category: otc | Type: HUMAN OTC DRUG LABEL
Date: 20231026

ACTIVE INGREDIENTS: BENZALKONIUM CHLORIDE 1.3 mg/1 g
INACTIVE INGREDIENTS: WATER; POLOXALENE; PEG-75 LANOLIN; GLYCERIN; POLYETHYLENE GLYCOL, UNSPECIFIED; LAURYL GLUCOSIDE; EDETATE DISODIUM ANHYDROUS; BRONOPOL; ALOE VERA LEAF

Rough and Smooth Heavy Duty Antiseptic Hand Sanitizer

Active ingredient

Benzalkonium chloride 0.13%

Purpose

Antiseptic

Use

- For hand washing to decrease bacteria on the skin

Warnings

For external use only

Do not use

in the eyes

Stop use and ask a doctor if

- irritation and redness develop.
- If condition persists for more than 72 hours consult a doctor.

Keep out of reach of children.

If swallowed, get medical help or contact a Poison Control Center right away.

Directions

- Peel back the foil seal and pull the center wipe through the slot in the lid.
- Wet hands thoroughly with product and allow to dry without wiping.
- Close lid after use to prevent wipes from drying out.

Inactive ingredients

Water, Estasol, Poloxalene, PEG-75 Lanolin, Glycerin, Aloe Barbadensis Extract, Polyethylene glycol, Lauryl Glycosides, Fragrance, Disodium EDTA, 2-bromo-2-nitropropane-1,3-diol, 1,2-benzisothiazolin-3-one.